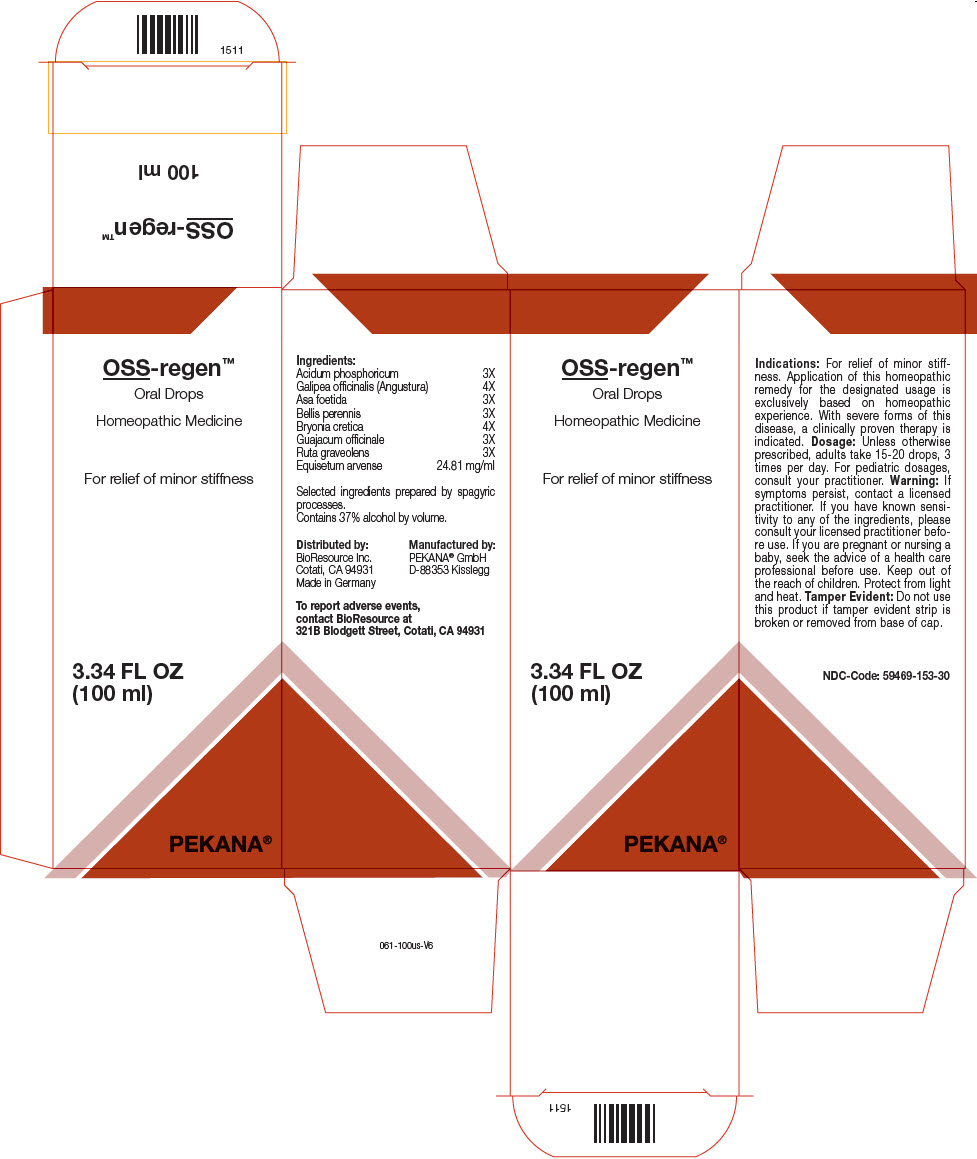 DRUG LABEL: OSS-regen
NDC: 59469-153 | Form: SOLUTION/ DROPS
Manufacturer: PEKANA Naturheilmittel GmbH
Category: homeopathic | Type: HUMAN OTC DRUG LABEL
Date: 20221216

ACTIVE INGREDIENTS: Phosphoric Acid 3 [hp_X]/100 mL; Angostura Bark 4 [hp_X]/100 mL; Ferula Assa-Foetida Resin 3 [hp_X]/100 mL; BELLIS PERENNIS WHOLE 3 [hp_X]/100 mL; Bryonia Dioica Root 4 [hp_X]/100 mL; Guaiacum officinale Resin 3 [hp_X]/100 mL; Ruta graveolens Flowering Top 3 [hp_X]/100 mL; Equisetum arvense Top 2481 mg/100 mL
INACTIVE INGREDIENTS: Water; Alcohol

OSS-regen™

ACTIVE INGREDIENT

Ingredients:
Acidum phosphoricum | 3X
Galipea officinalis (Angustura) | 4X
Asa foetida | 3X
Bellis perennis | 3X
Bryonia cretica | 4X
Guajacum officinale | 3X
Ruta graveolens | 3X
Equisetum arvense | 24.81 mg/ml

INACTIVE INGREDIENT

Selected ingredients prepared by spagyric processes.

Contains 37% alcohol by volume.

Indications

PURPOSE

For relief of minor stiffness. Application of this homeopathic remedy for the designated usage is exclusively based on homeopathic experience. With severe forms of this disease, a clinically proven therapy is indicated.

Dosage

Unless otherwise prescribed, adults take 15-20 drops, 3 times per day. For pediatric dosages, consult your practitioner.

Warning

If symptoms persist, contact a licensed practitioner. If you have known sensitivity to any of the ingredients, please consult your licensed practitioner before use. If you are pregnant or nursing a baby, seek the advice of a health care professional before use.

Keep out of the reach of children.

STORAGE AND HANDLING

Protect from light and heat.

Tamper Evident

Do not use this product if tamper evident strip is broken or removed from base of cap.

QUESTIONS

To report adverse events, contact BioResource at 321B Blodgett Street, Cotati, CA 94931

Manufactured by:
PEKANA® GmbH
D-88353 Kisslegg

Distributed by:
BioResource Inc.
Cotati, CA 94931

PRINCIPAL DISPLAY PANEL - 100 ml Bottle Box

OSS-regen™
Oral Drops

Homeopathic Medicine

For relief of minor stiffness

3.34 FL OZ
(100 ml)

PEKANA®